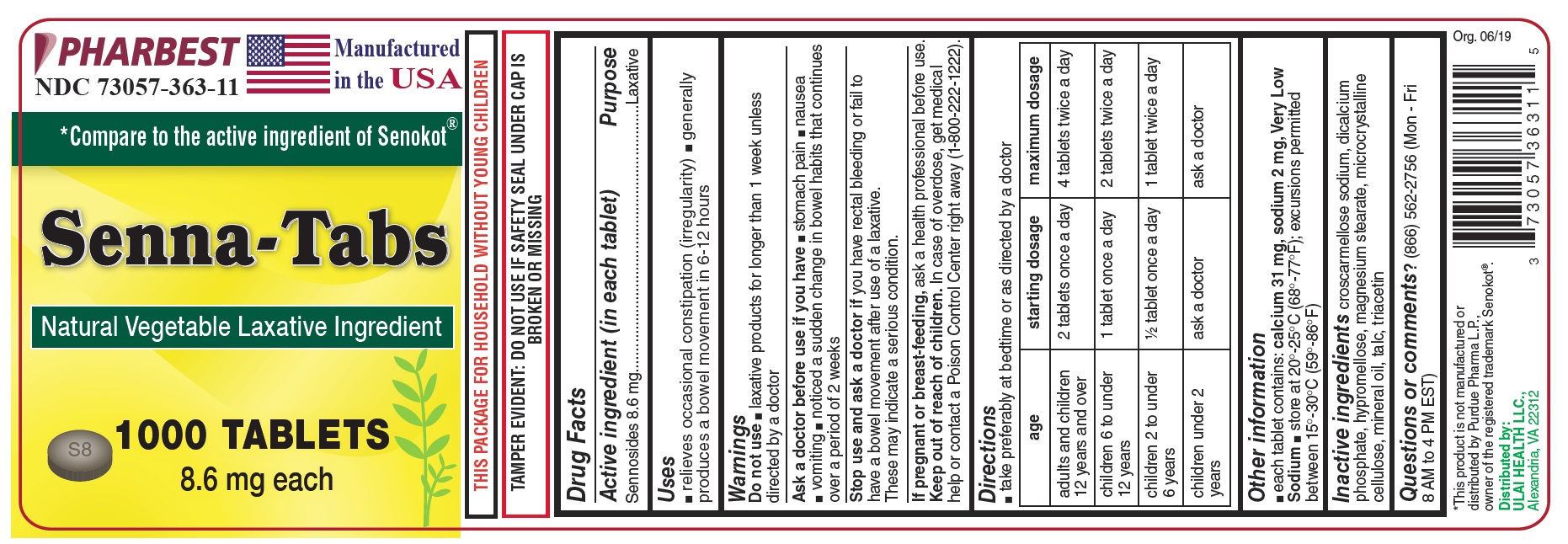 DRUG LABEL: Senna-Tabs
NDC: 73057-363 | Form: TABLET, FILM COATED
Manufacturer: Ulai Health LLC
Category: otc | Type: HUMAN OTC DRUG LABEL
Date: 20250120

ACTIVE INGREDIENTS: SENNOSIDES 8.6 mg/1 1
INACTIVE INGREDIENTS: CALCIUM PHOSPHATE, DIBASIC, ANHYDROUS; HYPROMELLOSE, UNSPECIFIED; MAGNESIUM STEARATE; CELLULOSE, MICROCRYSTALLINE; MINERAL OIL; TALC; TRIACETIN; CROSCARMELLOSE SODIUM

Drug Facts

Active ingredient (in each tablet)

Sennosides 8.6mg

Purpose

Laxative

Uses

- relieves occasional constipation (irregularity)
- generally produces a bowel movement in 6-12 hours

Warnings

Do not use

- laxative products for longer than 1 week unless directed by a doctor

Ask a doctor before use if you have

- stomach pain
- nausea
- vomiting
- noticed a sudden change in bowel habits that continues over a period of 2 weeks

Stop use and ask a doctor if

you have rectal bleeding or fail to have a bowel movement after the use of a laxative.

These may indicate a serious condition.

If pregnant or breast feeding,

ask a health professional before use.

Keep out of reach of children.

In case of overdose, get medical help or contact a Poison Control Center right away (1-800-222-1222).

Directions

- take preferably at bedtime or as directed by a doctor

age | starting dosage | maximum dosage
adults and children 12 years and over | 2 tablets once a day | 4 tablets twice a day
children 6 to under 12 years | 1 tablet once a day | 2 tablets twice a day
children 2 to under 6 years | ½ tablet once a day | 1 tablet twice a day
children under 2 years | ask a doctor | ask a doctor

Other information

- each tablet contains: calcium 31 mg, sodium 2 mg, Very Low Sodium
- store at 20^0-25^0C (68^0-77^0F); excursions permitted between 15^0-30^0C (59^0-86^0F)

Inactive ingredients

croscarmellose sodium, dicalcium phosphate, hypromellose, magnesium stearate, microcrystalline cellulose, mineral oil, talc, triacetin

Questions or comments?

(866) 562-2756 (Mon - Fri 8 AM to 4 PM EST)

PACKAGE LABEL

PHARBEST

NDC 73057-363-11

Manufactured in the USA

*Compare to the active ingredient of Senokot®

Senna-Tabs

Natural Vegetable Laxative Ingredient

1000 TABLETS

8.6 mg each